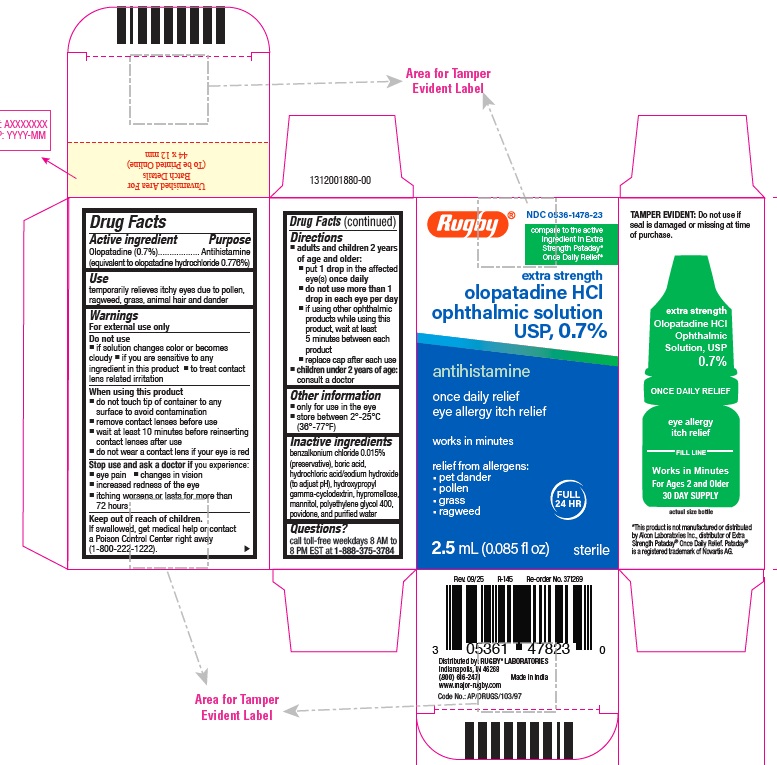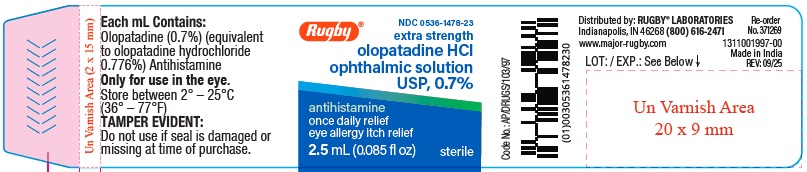 DRUG LABEL: Olopatadine HCl
NDC: 0536-1478 | Form: SOLUTION/ DROPS
Manufacturer: Rugby Laboratories
Category: otc | Type: Human OTC Drug Label
Date: 20260122

ACTIVE INGREDIENTS: OLOPATADINE HYDROCHLORIDE 7 mg/1 mL
INACTIVE INGREDIENTS: BENZALKONIUM CHLORIDE; BORIC ACID; HYDROCHLORIC ACID; HYDROXYPROPYL .GAMMA.-CYCLODEXTRIN; HYPROMELLOSE 2910 (4000 MPA.S); MANNITOL; POLYETHYLENE GLYCOL 400; POVIDONE K30; SODIUM HYDROXIDE; WATER

ACTIVE INGREDIENT

Olopatadine (0.7%) (equivalent to olopatadine hydrochloride 0.776%)

PURPOSE

Antihistamine

USE

temporarily relieves itchy eyes due to pollen, ragweed, grass, animal hair and dander

WARNINGS

For external use only

DO NOT USE

• if solution changes color or becomes cloudy
• if you are sensitive to any ingredient in this product
• to treat contact lens related irritation

WHEN USING THIS PRODUCT

• do not touch tip of container to any surface to avoid contamination
• remove contact lenses before use
• wait at least 10 minutes before reinserting contact lenses after use
• do not wear a contact lens if your eye is red

STOP USE AND ASK DOCTOR IF

you experience:

- eye pain
- changes in vision
- increased redness of the eye
- itching worsens or lasts for more than 72 hours

KEEP OUT OF REACH OF CHILDREN

If swallowed, get medical help or contact a Poison Control Center right away(1-800-222-1222).

DIRECTIONS

- adults and children 2 years of age and older:
- put 1 drop in the affected eye(s) once daily
- do not use more than 1 drop in each eye per day
- if using other ophthalmic products while using this product, wait at least 5 minutes between each product
- replace cap after each use
- children under 2 years of age: consult a doctor

OTHER INFORMATION

• only for use in the eye
• store between 2° to 25°C (36° to 77°F)

INACTIVE INGREDIENTS

benzalkonium chloride 0.015% (preservative), boric acid, hydrochloric acid/sodium hydroxide (to adjust pH), hydroxypropyl gamma cyclodextrin, hypromellose, mannitol, polyethylene glycol 400, povidone and purified water.

QUESTIONS?

call toll-free weekdays 8 AM to 8 PM EST at 1-888-375-3784

Distributed by:

RUGBY® LABORATORIES

Indianapolis, IN 46268

(800) 616-2471

www.major-rugby.com

Made in India

Rev. 09/25 R-145 Re-order No. 371269

*This product is not manufactured or distributed by Alcon Laboratories Inc., distributor of Extra Strength Pataday® Once Daily Relief . Pataday® is a registered trademark of Novartis AG.

PRINCIPAL DISPLAY PANEL

Carton Label:

NDC 0536-1478-23
extra strength

olopatadine HCl
ophthalmic solution USP, 0.7%
antihistamine

once daily relief

eye allergy itch relief

works in minutes

FULL 24 HR

relief from allergens:

• pet dander

• pollen

• grass

• ragweed

2.5 mL (0.085 fl oz)
sterile

Compare to active ingredient in Extra Strength Pataday Once Daily Relief*

Tamper Evident: Do not use if seal is damaged or missing at time of purchase.

For Ages 2 and Older

30 DAY SUPPLY

Bottle Label:
extra strength

olopatadine HCl
ophthalmic solution USP, 0.7%
antihistamine

once daily relief

eye allergy itch relief
2.5 mL (0.085 fl oz)
sterile